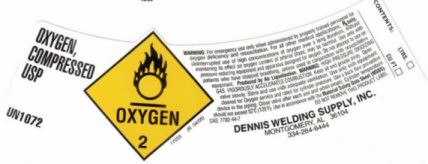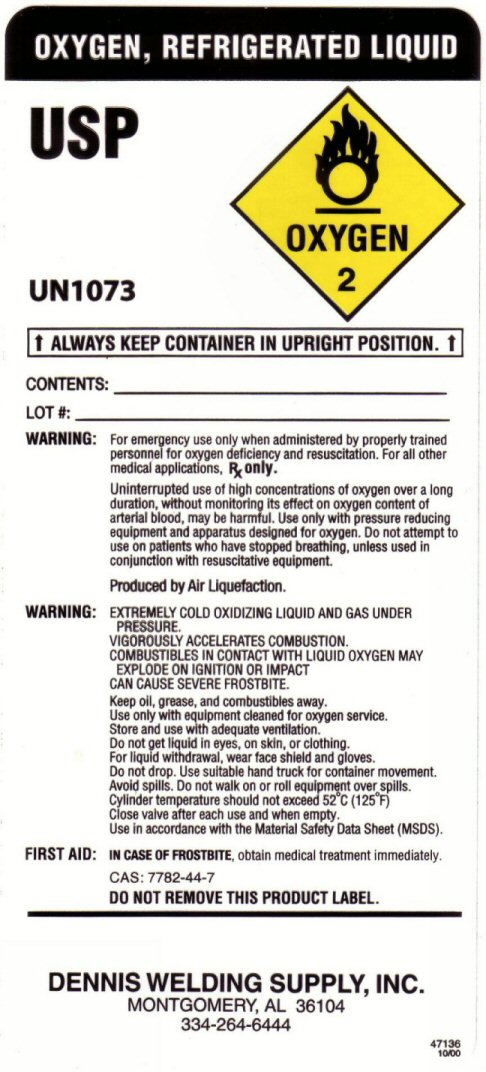 DRUG LABEL: OXYGEN
NDC: 53720-001 | Form: GAS
Manufacturer: Dennis Welding Supply, Inc.
Category: prescription | Type: HUMAN PRESCRIPTION DRUG LABEL
Date: 20251212

ACTIVE INGREDIENTS: OXYGEN 99 L/100 L

OXYGEN COMPRESSED LABEL

OXYGEN COMPRESSED USP UN 1072 OXYGEN-2 WARNING: FOR EMERGENCY USE ONLY WHEN ADMINISTERED BY PROPERLY TRAINED PERSONNEL FOR OXYGEN DEFICIENCY AND RESUSCITATION. FOR ALL OTHER APPLICATIONS Rx ONLY. UNINTERRUPTED USE OF HIGH CONCENTRATIONS OF OXYGEN OVER A LONG DURATION WITHOUT MONITORING ITS EFFECT ON OXYGEN CONTENT OF ARTERIAL BLOOD MAY BE HARMFUL. USE ONLY WITH PRESSURE REDUCING EQUIPMENT AND APPARATUS DESIGNED FOR OXYGEN. DO NOT ATTEMPT TO USE ON PATIENTS WHO HAVE STOPPED BREATHING UNLESS USED IN CONJUNCTION WITH RESUSCITATIVE EQUIPMENT. PRODUCED BY AIR LIQUEFACTION. WARNING: HIGH PRESSURE GAS VIGOROUSLY ACCELERATES COMBUSTION. KEEP OIL AND GREASE AWAY. OPEN VALVE SLOWLY. STORE AND USE WITH ADEQUATE VENTILATION. USE ONLY WITH EQUIPMENT CLEANED FOR OXYGEN SERVICE AND RATED FOR CYLINDER PRESSURE. USE A BACK FLOW PREVENTATIVE DEVICE IN THE PIPING. CLOSE VALVE AFTER EACH USE AND WHEN EMPTY. CYLINDER TEMPERATURE SHOULD NOT EXCEED 52 C (125 F) USE IN ACCORDANCE WITH THE MATERIAL SAFETY DATA SHEET (MSDS)

res

OXYGEN REFRIGERATED LIQUID LABEL

OXYGEN REFRIGERATED LIQUID U.S.P. UN 1073 CRYOGENIC LIQUID PRODUCED BY AIR LIQUEFACTION OXYGEN-2 ALWAYS KEEP CONTAINER IN UPRIGHT POSITION WARNING: EXTREMELY COLD OXIDIZING LIQUID AND GAS UNDER PRESSURE. VIGOROUSLY ACCELERATES COMBUSTION. COMBUSTIBLES IN CONTACT WITH LIQUID OXYGEN MAY EXPLODE ON IGNITION OR IMPACT. CAN CAUSE SEVERE FROSTBITE. FOR EMERGENCY USE ONLY WHEN ADMINISTERED BY PROPERLY TRAINED PERSONNEL FOR OXYGEN DEFICIENCY AND RESUSCITATION. FOR ALL OTHER MEDICAL APPLICATIONS Rx ONLY. WARNING: CAUTION FEDERAL LAW PROHIBITS DISPENSING WITHOUT A PRESCRIPTION. DO NOT REMOVE THIS PRODUCT LABEL
WARNING: UNINTERRUPTED USE OF HIGH CONCENTRATIONS OF OXYGEN OVER LONG DURATION, WITHOUT MONITORING ITS EFFECT ON OXYGEN CONTENT OF ARTERIAL BLOOD MAY BE HARMFUL. USE ONLY WITH PRESSURE REDUCING EQUIPMENT AND APPARATUS DESIGNED FOR OXYGEN. DO NOT ATTEMPT TO USE ON PATIENTS WHO HAVE STOPPED BREATHING UNLESS USED IN CONJUNCTION WITH RESUSCITATIVE EQUIPMENT. KEEP OIL, GREASE, AND COMBUSTIBLES AWAY. USE ONLY WITH EQUIPMENT CLEANED FOR OXYGEN SERVICE. STORE AND USE WITH ADEQUATE VENTILATION. DO NOT GET LIQUID IN EYES, ON SKIN OR CLOTHING. FOR LIQUID WITHDRAWAL WEAR FACE SHIELD AND GLOVES. DO NOT DROP. USE HAND TRUCK FOR CONTAINER MOVEMENT. AVOID SPILLS. DO NOT WALK OR ROLL EQUIPMENT OVER SPILLS. CLOSE VALVE AFTER EACH USE AND WHEN EMPTY. USE IN ACCORDANCE WITH THE MATERIAL SAFETY DATA SHEET. IN CASE OF FROSTBITE OBTAIN MEDICAL TREATMENT IMMEDIATELY.

res